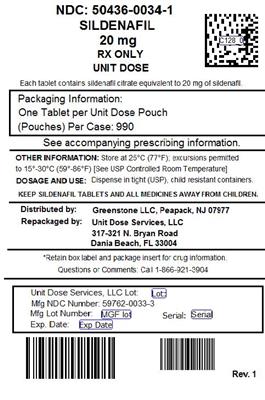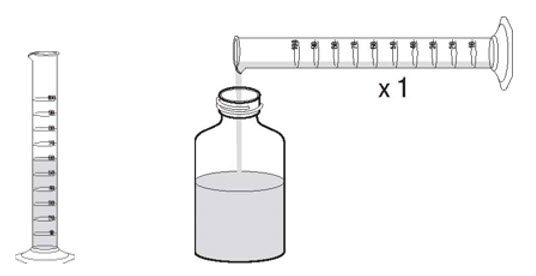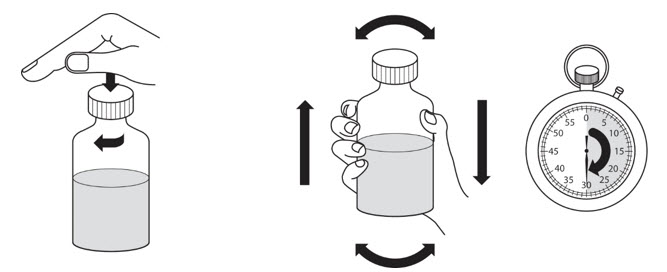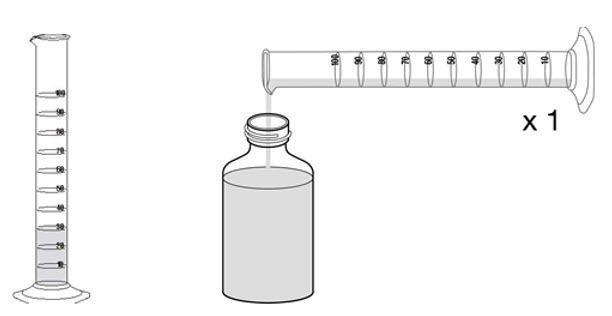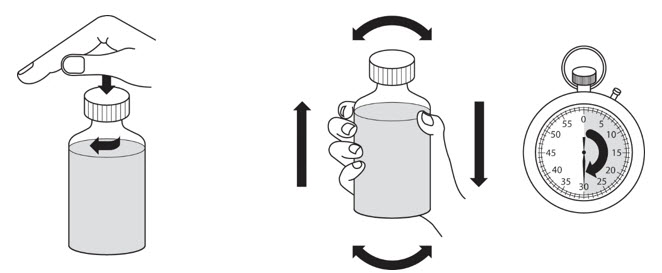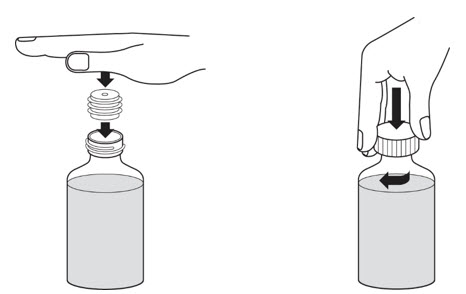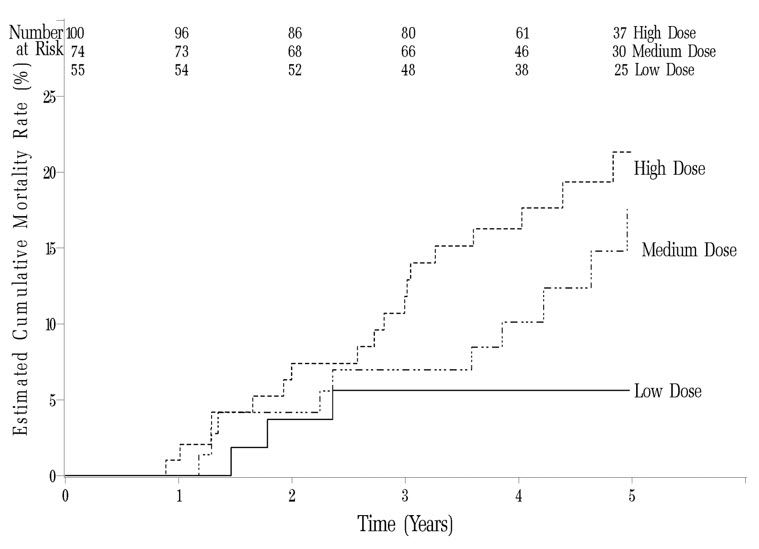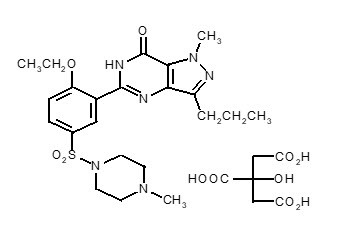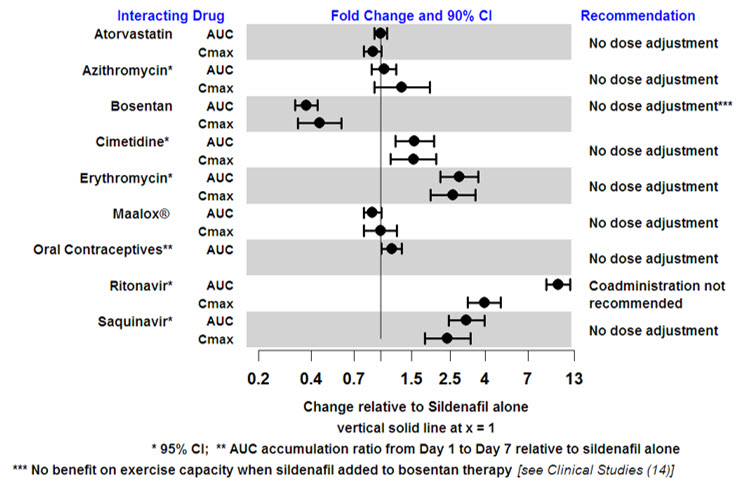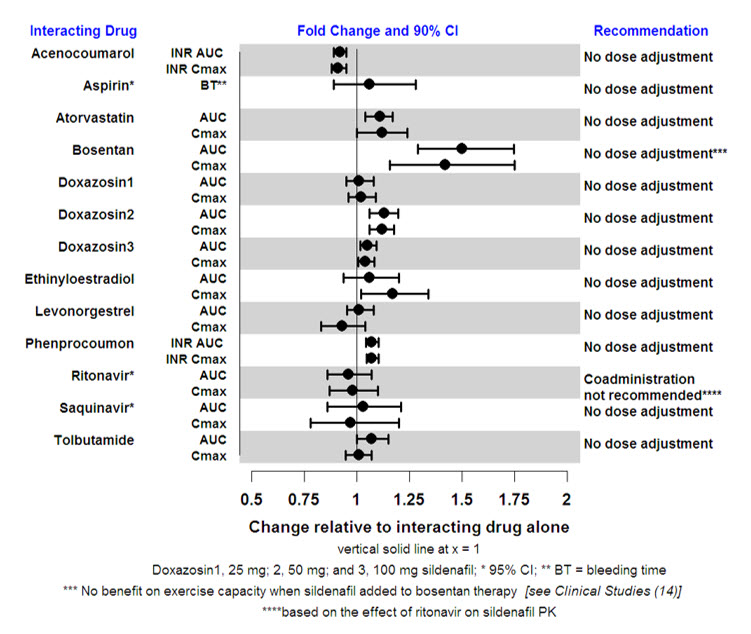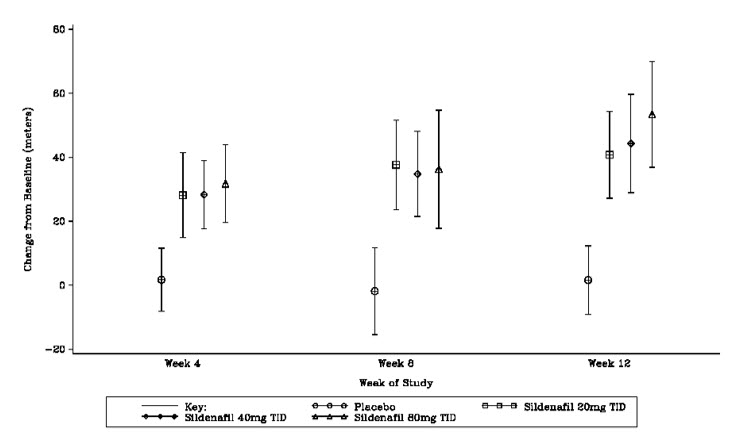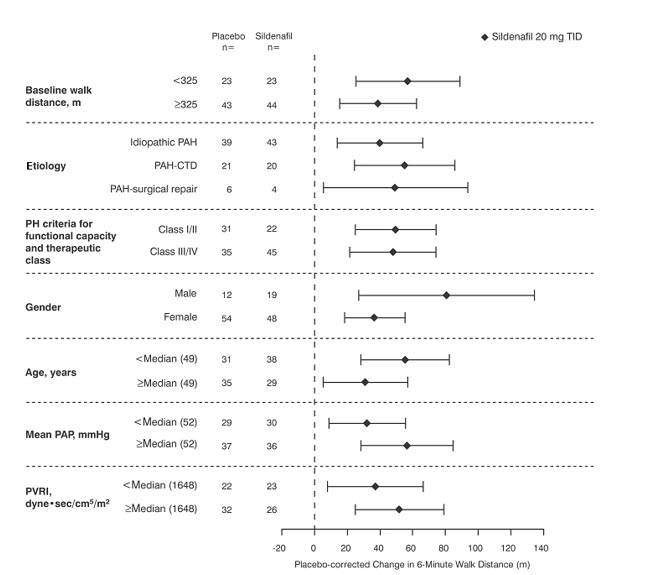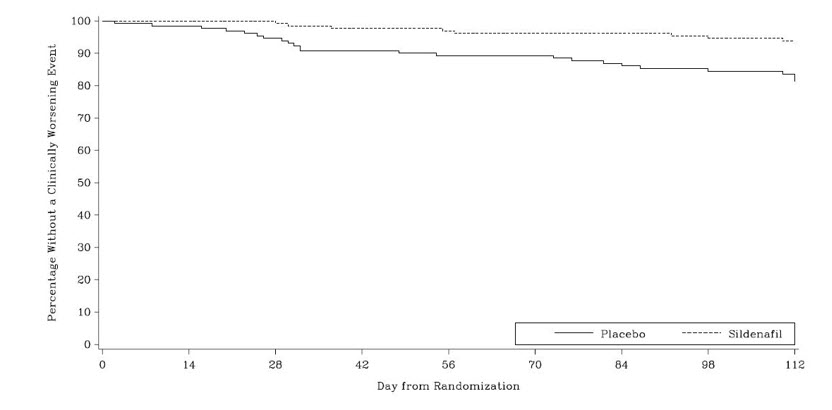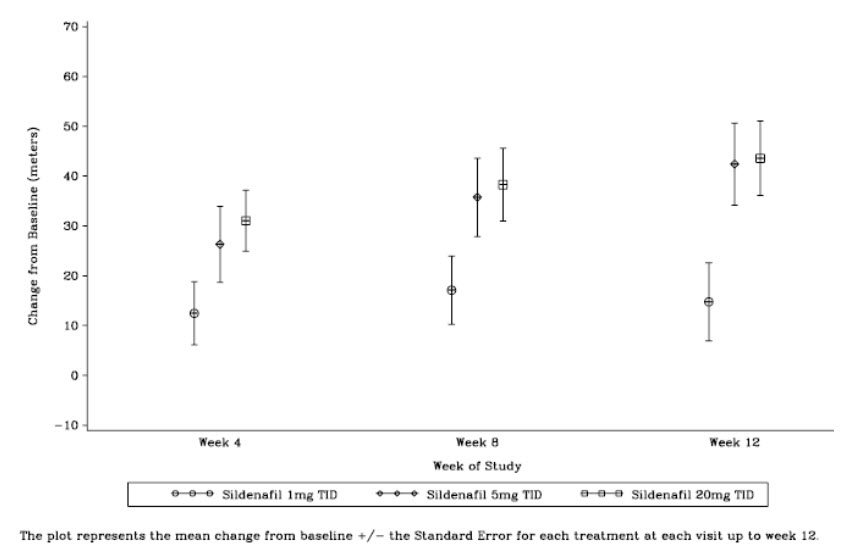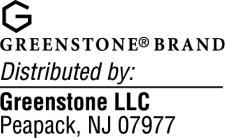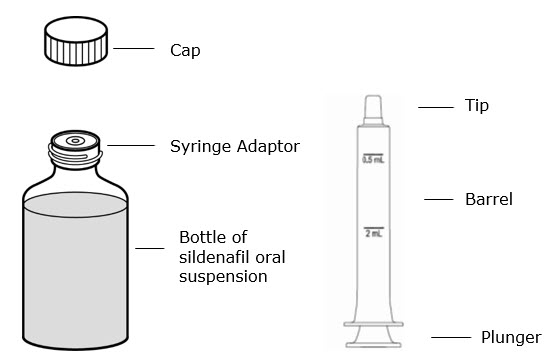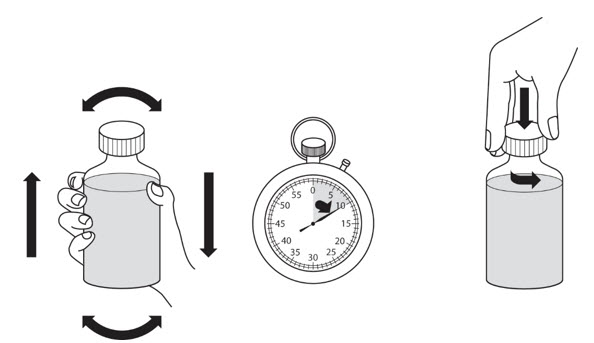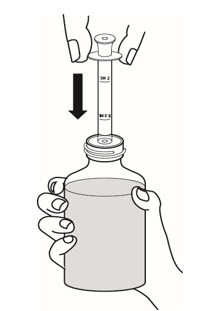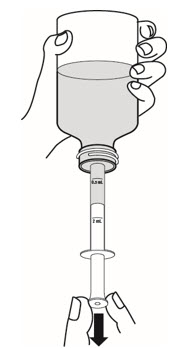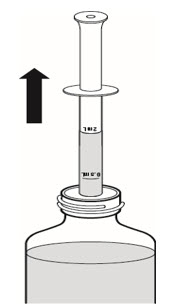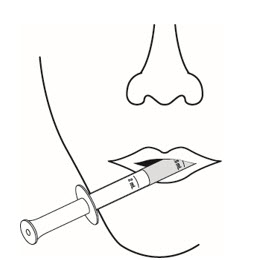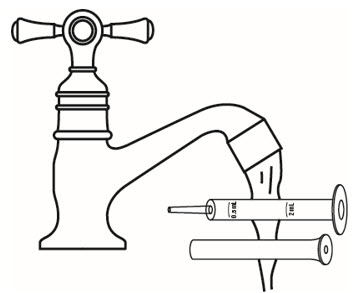 DRUG LABEL: Sildenafil
NDC: 50436-0034 | Form: TABLET, FILM COATED
Manufacturer: Unit Dose Services
Category: prescription | Type: HUMAN PRESCRIPTION DRUG LABEL
Date: 20220314

ACTIVE INGREDIENTS: SILDENAFIL CITRATE 20 mg/1 1
INACTIVE INGREDIENTS: MICROCRYSTALLINE CELLULOSE; ANHYDROUS DIBASIC CALCIUM PHOSPHATE; CROSCARMELLOSE SODIUM; MAGNESIUM STEARATE; HYPROMELLOSE, UNSPECIFIED; TITANIUM DIOXIDE; LACTOSE MONOHYDRATE; TRIACETIN

HIGHLIGHTS OF PRESCRIBING INFORMATION

These highlights do not include all the information needed to use sildenafil safely and effectively. See full prescribing information for sildenafil.
Sildenafil tablets, for oral use
Sildenafil for oral suspension
Initial U.S. Approval: 1998

1 INDICATIONS AND USAGE

Sildenafil is a phosphodiesterase-5 (PDE-5) inhibitor indicated for the treatment of pulmonary arterial hypertension (PAH) (WHO Group I) in adults to improve exercise ability and delay clinical worsening. Studies establishing effectiveness were short-term (12 to 16 weeks), and included predominately patients with NYHA Functional Class II–III symptoms. Etiologies were idiopathic (71%) or associated with connective tissue disease (25%). (1)

Limitation of Use: Adding sildenafil to bosentan therapy does not result in any beneficial effect on exercise capacity. (1, 14)

2 DOSAGE AND ADMINISTRATION

- Tablets and oral suspension: 5 mg or 20 mg three times a day, 4–6 hours apart; see full prescribing information for reconstitution instructions for the Powder for Oral Suspension (2.1, 2.2)

3 DOSAGE FORMS AND STRENGTHS

- Tablets: 20 mg (3)
- For Oral Suspension: 10 mg/mL (when reconstituted) (3)

4 CONTRAINDICATIONS

- Use with organic nitrates or riociguat. (4)
- History of hypersensitivity reaction to sildenafil or any component of the tablet or oral suspension. (4)

5 WARNINGS AND PRECAUTIONS

- Increased mortality with increasing doses in pediatric patients. Not recommended for use in pediatric patients. (5.1)
- Vasodilation effects may be more common in patients with hypotension or on antihypertensive therapy. (5.2)
- Use in pulmonary veno-occlusive disease may cause pulmonary edema and is not recommended. (5.3)
- Hearing or visual impairment: Seek medical attention if sudden decrease or loss of vision or hearing occurs. (5.5, 5.6)
- Pulmonary hypertension secondary to sickle cell disease: sildenafil may cause serious vaso-occlusive crises. (5.9)

6 ADVERSE REACTIONS

Most common adverse reactions greater than or equal to 3% and more frequent than placebo were epistaxis, headache, dyspepsia, flushing, insomnia, erythema, dyspnea, and rhinitis. (6.1, 6.2)

To report SUSPECTED ADVERSE REACTIONS, contact Greenstone LLC at 1-800-438-1985 or FDA at 1-800-FDA-1088 or www.fda.gov/medwatch.

7 DRUG INTERACTIONS

- Concomitant alpha-blockers or amlodipine: Note additive blood pressure lowering effects. (7)
- Use with ritonavir and other potent CYP3A inhibitors: Not recommended. (7, 12.3)
- Concomitant PDE-5 inhibitors: Avoid use with Viagra or other PDE-5 inhibitors. (5.7)

FULL PRESCRIBING INFORMATION

1 INDICATIONS AND USAGE

Sildenafil is indicated for the treatment of pulmonary arterial hypertension (WHO Group I) in adults to improve exercise ability and delay clinical worsening. The delay in clinical worsening was demonstrated when sildenafil was added to background epoprostenol therapy [see Clinical Studies (14)].

Studies establishing effectiveness were short-term (12 to 16 weeks), and included predominately patients with New York Heart Association (NYHA) Functional Class II–III symptoms and idiopathic etiology (71%) or associated with connective tissue disease (CTD) (25%).

Limitation of Use: Adding sildenafil to bosentan therapy does not result in any beneficial effect on exercise capacity [see Clinical Studies (14)].

2 DOSAGE AND ADMINISTRATION

2.1 Sildenafil Tablets and Oral Suspension

The recommended dose of sildenafil is 5 mg or 20 mg three times a day. Administer sildenafil doses 4–6 hours apart.

In the clinical trial no greater efficacy was achieved with the use of higher doses. Treatment with doses higher than 20 mg three times a day is not recommended.

2.2 Reconstitution of the Powder for Oral Suspension

Note: Reconstitute the contents of the bottle with a total volume of 90 mL (60 mL followed by 30 mL). Refer to the detailed instructions below.

1. Tap the bottle to release the powder.
2. Remove the cap.
3. Accurately measure out 60 mL of water and pour the water into the bottle. (Figure 1)
  Figure 1
4. Replace the cap and shake the bottle vigorously for a minimum of 30 seconds. (Figure 2)
  Figure 2
5. Remove the cap.
6. Accurately measure out another 30 mL of water and add this to the bottle. You should always add a total of 90 mL of water irrespective of the dose prescribed. (Figure 3)
  Figure 3
7. Replace the cap and shake the bottle vigorously for a minimum of 30 seconds. (Figure 4)
  Figure 4
8. Remove the cap.
9. Press the bottle adaptor into the neck of the bottle (as shown on Figure 5, below). The adaptor is provided so that you can fill the oral syringe with medicine from the bottle. Replace the cap on the bottle.
  Figure 5
10. Write the expiration date of the reconstituted oral suspension on the bottle label (the expiration date of the reconstituted oral suspension is 60 days from the date of reconstitution).

Incompatibilities

Do not mix with any other medication or additional flavoring agent.

3 DOSAGE FORMS AND STRENGTHS

Sildenafil Tablets

White, film-coated, round tablets engraved with "SDF20" containing sildenafil citrate equivalent to 20 mg of sildenafil.

Sildenafil for Oral Suspension

White to off-white powders containing 1.57 g of sildenafil citrate (equivalent to 1.12 g of sildenafil) in a bottle intended for reconstitution. Following reconstitution with 90 mL of water, the volume of the oral suspension is 112 mL and the oral suspension contains 10 mg/mL sildenafil. A 2 mL oral syringe (with 0.5 mL and 2 mL dose markings) and a press-in bottle adaptor are also provided.

4 CONTRAINDICATIONS

Sildenafil is contraindicated in patients with:

- Concomitant use of organic nitrates in any form, either regularly or intermittently, because of the greater risk of hypotension [see Warnings and Precautions (5.2)].
- Concomitant use of riociguat, a guanylate cyclase stimulator. PDE-5 inhibitors, including sildenafil, may potentiate the hypotensive effects of riociguat.
- Known hypersensitivity to sildenafil or any component of the tablet or oral suspension. Hypersensitivity, including anaphylactic reaction, anaphylactic shock and anaphylactoid reaction, has been reported in association with the use of sildenafil.

5 WARNINGS AND PRECAUTIONS

5.1 Mortality with Pediatric Use

In a long-term trial in pediatric patients with PAH, an increase in mortality with increasing sildenafil dose was observed. Deaths were first observed after about 1 year and causes of death were typical of patients with PAH. Use of sildenafil, particularly chronic use, is not recommended in children [see Use in Specific Populations (8.4)].

5.2 Hypotension

Sildenafil has vasodilatory properties, resulting in mild and transient decreases in blood pressure. Before prescribing sildenafil, carefully consider whether patients with certain underlying conditions could be adversely affected by such vasodilatory effects (e.g., patients on antihypertensive therapy or with resting hypotension [BP less than 90/50], fluid depletion, severe left ventricular outflow obstruction, or autonomic dysfunction). Monitor blood pressure when co-administering blood pressure lowering drugs with sildenafil.

5.3 Worsening Pulmonary Vascular Occlusive Disease

Pulmonary vasodilators may significantly worsen the cardiovascular status of patients with pulmonary veno-occlusive disease (PVOD). Since there are no clinical data on administration of sildenafil to patients with veno-occlusive disease, administration of sildenafil to such patients is not recommended. Should signs of pulmonary edema occur when sildenafil is administered, consider the possibility of associated PVOD.

5.4 Epistaxis

The incidence of epistaxis was 13% in patients taking sildenafil with PAH secondary to CTD. This effect was not seen in idiopathic PAH (sildenafil 3%, placebo 2%) patients. The incidence of epistaxis was also higher in sildenafil-treated patients with a concomitant oral vitamin K antagonist (9% versus 2% in those not treated with concomitant vitamin K antagonist).

The safety of sildenafil is unknown in patients with bleeding disorders or active peptic ulceration.

5.5 Visual Loss

When used to treat erectile dysfunction, non-arteritic anterior ischemic optic neuropathy (NAION), a cause of decreased vision including permanent loss of vision, has been reported postmarketing in temporal association with the use of phosphodiesterase type 5 (PDE-5) inhibitors, including sildenafil. Most, but not all, of these patients had underlying anatomic or vascular risk factors for developing NAION, including but not necessarily limited to: low cup to disc ratio ("crowded disc"), age over 50, diabetes, hypertension, coronary artery disease, hyperlipidemia and smoking. Based on published literature, the annual incidence of NAION is 2.5–11.8 cases per 100,000 males aged ≥ 50 per year in the general population.

An observational case-crossover study evaluated the risk of NAION when PDE-5 inhibitor use, as a class, occurred immediately before NAION onset (within 5 half-lives), compared to PDE-5 inhibitor use in a prior time period. The results suggest an approximate 2-fold increase in the risk of NAION, with a risk estimate of 2.15 (95% CI 1.06, 4.34). A similar study reported a consistent result, with a risk estimate of 2.27 (95% CI 0.99, 5.20). Other risk factors for NAION, such as the presence of "crowded" optic disc, may have contributed to the occurrence of NAION in these studies.

Neither the rare postmarketing reports, nor the association of PDE-5 inhibitor use and NAION in the observational studies, substantiate a causal relationship between PDE-5 inhibitor use and NAION [see Adverse Reactions (6.2].

Advise patients to seek immediate medical attention in the event of a sudden loss of vision in one or both eyes while taking PDE-5 inhibitors, including sildenafil. Physicians should also discuss the increased risk of NAION with patients who have already experienced NAION in one eye, including whether such individuals could be adversely affected by use of vasodilators, such as PDE-5 inhibitors.

There are no controlled clinical data on the safety or efficacy of sildenafil in patients with retinitis pigmentosa, a minority whom have genetic disorders of retinal phosphodiesterases. Prescribe sildenafil with caution in these patients.

5.6 Hearing Loss

Cases of sudden decrease or loss of hearing, which may be accompanied by tinnitus and dizziness, have been reported in temporal association with the use of PDE-5 inhibitors, including sildenafil. In some of the cases, medical conditions and other factors were reported that may have played a role. In many cases, medical follow-up information was limited. It is not possible to determine whether these reported events are related directly to the use of sildenafil, to the patient's underlying risk factors for hearing loss, a combination of these factors, or to other factors.

Advise patients to seek prompt medical attention in the event of sudden decrease or loss of hearing while taking PDE-5 inhibitors, including sildenafil.

5.7 Combination with other PDE-5 inhibitors

Sildenafil is also marketed as VIAGRA®. The safety and efficacy of combinations of sildenafil with VIAGRA or other PDE-5 inhibitors have not been studied. Inform patients taking sildenafil not to take VIAGRA or other PDE-5 inhibitors.

5.8 Priapism

Use sildenafil with caution in patients with anatomical deformation of the penis (e.g., angulation, cavernosal fibrosis, or Peyronie's disease) or in patients who have conditions, which may predispose them to priapism (e.g., sickle cell anemia, multiple myeloma, or leukemia). In the event of an erection that persists longer than 4 hours, the patient should seek immediate medical assistance. If priapism (painful erection greater than 6 hours in duration) is not treated immediately, penile tissue damage and permanent loss of potency could result.

5.9 Vaso-occlusive Crisis in Patients with Pulmonary Hypertension Secondary to Sickle Cell Anemia

In a small, prematurely terminated study of patients with pulmonary hypertension (PH) secondary to sickle cell disease, vaso-occlusive crises requiring hospitalization were more commonly reported by patients who received sildenafil than by those randomized to placebo. The effectiveness and safety of sildenafil in the treatment of PAH secondary to sickle cell anemia has not been established.

6 ADVERSE REACTIONS

The following serious adverse events are discussed elsewhere in the labeling:

- Mortality with pediatric use [see Warnings and Precautions (5.1) and Use in Specific Populations (8.4)]
- Hypotension [see Warnings and Precautions (5.2)]
- Vision loss [see Warnings and Precautions (5.5)]
- Hearing loss [see Warnings and Precautions (5.6)]
- Priapism [see Warnings and Precautions (5.8)]
- Vaso-occlusive crisis [see Warnings and Precautions (5.9)]

6.1 Clinical Trials Experience

Because clinical trials are conducted under widely varying conditions, adverse reaction rates observed in the clinical trials of a drug cannot be directly compared to rates in the clinical trials of another drug and may not reflect the rates observed in practice.

Safety data of sildenafil in adults were obtained from the 12-week, placebo-controlled clinical study (Study 1) and an open-label extension study in 277 sildenafil-treated patients with PAH, WHO Group I [see Clinical Studies (14)].

The overall frequency of discontinuation in sildenafil-treated patients on 20 mg three times a day was 3% and was the same for the placebo group.

In Study 1, the adverse reactions that were reported by at least 3% of sildenafil-treated patients (20 mg three times a day) and were more frequent in sildenafil-treated patients than in placebo-treated patients, are shown in Table 1. Adverse reactions were generally transient and mild to moderate in nature.

Table 1. Most Common Adverse Reactions in Patients with PAH in Study 1 (More Frequent in Sildenafil-Treated Patients than Placebo-Treated Patients and Incidence ≥3% in Sildenafil-Treated Patients)
 | Placebo, % (n = 70) | Sildenafil 20 mg three times a day, % (n = 69) | Placebo-Subtracted, %
Epistaxis | 1 | 9 | 8
Headache | 39 | 46 | 7
Dyspepsia | 7 | 13 | 6
Flushing | 4 | 10 | 6
Insomnia | 1 | 7 | 6
Erythema | 1 | 6 | 5
Dyspnea exacerbated | 3 | 7 | 4
Rhinitis | 0 | 4 | 4
Diarrhea | 6 | 9 | 3
Myalgia | 4 | 7 | 3
Pyrexia | 3 | 6 | 3
Gastritis | 0 | 3 | 3
Sinusitis | 0 | 3 | 3
Paresthesia | 0 | 3 | 3

At doses higher than the recommended 20 mg three times a day, there was a greater incidence of some adverse reactions including flushing, diarrhea, myalgia and visual disturbances. Visual disturbances were identified as mild and transient, and were predominately color-tinge to vision, but also increased sensitivity to light or blurred vision.

The incidence of retinal hemorrhage with sildenafil 20 mg three times a day was 1.4% versus 0% placebo and for all sildenafil doses studied was 1.9% versus 0% placebo. The incidence of eye hemorrhage at both 20 mg three times a day and at all doses studied was 1.4% for sildenafil versus 1.4% for placebo. The patients experiencing these reactions had risk factors for hemorrhage including concurrent anticoagulant therapy.

In a placebo-controlled fixed dose titration study (Study 2) of sildenafil (starting with recommended dose of 20 mg and increased to 40 mg and then 80 mg all three times a day) as an adjunct to intravenous epoprostenol in patients with PAH, the adverse reactions that were more frequent in the sildenafil + epoprostenol group than in the epoprostenol group (greater than 6% difference) are shown in Table 2 [see Clinical Studies (14)].

Table 2. Adverse Reactions (%) in patients with PAH in Study 2 (incidence in Sildenafil + Epoprostenol group at least 6% greater than Epoprostenol group)
 | Sildenafil + Epoprostenol (n = 134) | Epoprostenol (n = 131) | (Sildenafil + Epoprostenol) minus Epoprostenol
Headache | 57 | 34 | 23
Edema [includes peripheral edema] | 25 | 13 | 14
Dyspepsia | 16 | 2 | 14
Pain in extremity | 17 | 6 | 11
Diarrhea | 25 | 18 | 7
Nausea | 25 | 18 | 7
Nasal congestion | 9 | 2 | 7

6.2 Postmarketing Experience

The following adverse reactions have been identified during post approval use of sildenafil (marketed for both PAH and erectile dysfunction). Because these reactions are reported voluntarily from a population of uncertain size, it is not always possible to reliably estimate their frequency or establish a causal relationship to drug exposure.

Cardiovascular Events

In postmarketing experience with sildenafil at doses indicated for erectile dysfunction, serious cardiovascular, cerebrovascular, and vascular events, including myocardial infarction, sudden cardiac death, ventricular arrhythmia, cerebrovascular hemorrhage, transient ischemic attack, hypertension, pulmonary hemorrhage, and subarachnoid and intracerebral hemorrhages have been reported in temporal association with the use of the drug. Most, but not all, of these patients had preexisting cardiovascular risk factors. Many of these events were reported to occur during or shortly after sexual activity, and a few were reported to occur shortly after the use of sildenafil without sexual activity. Others were reported to have occurred hours to days after use concurrent with sexual activity. It is not possible to determine whether these events are related directly to sildenafil, to sexual activity, to the patient's underlying cardiovascular disease, or to a combination of these or other factors.

Nervous system

Seizure, seizure recurrence.

Ophthalmologic

NAION [see Warnings and Precautions (5.5) and Patient Counseling Information (17)].

7 DRUG INTERACTIONS

Nitrates

Concomitant use of sildenafil with nitrates in any form is contraindicated [see Contraindications (4)].

Ritonavir and other Potent CYP3A Inhibitors

Concomitant use of sildenafil with ritonavir and other potent CYP3A inhibitors is not recommended [see Clinical Pharmacology (12.3)].

Other drugs that reduce blood pressure

Alpha blockers. In drug-drug interaction studies, sildenafil (25 mg, 50 mg, or 100 mg) and the alpha-blocker doxazosin (4 mg or 8 mg) were administered simultaneously to patients with benign prostatic hyperplasia (BPH) stabilized on doxazosin therapy. In these study populations, mean additional reductions of supine systolic and diastolic blood pressure of 7/7 mmHg, 9/5 mmHg, and 8/4 mmHg, respectively, were observed. Mean additional reductions of standing blood pressure of 6/6 mmHg, 11/4 mmHg, and 4/5 mmHg, respectively, were also observed. There were infrequent reports of patients who experienced symptomatic postural hypotension. These reports included dizziness and light-headedness, but not syncope.

Amlodipine. When sildenafil 100 mg oral was co-administered with amlodipine, 5 mg or 10 mg oral, to hypertensive patients, the mean additional reduction on supine blood pressure was 8 mmHg systolic and 7 mmHg diastolic.

Monitor blood pressure when co-administering blood pressure lowering drugs with sildenafil [see Warnings and Precautions (5.2)].

8 USE IN SPECIFIC POPULATIONS

8.1 Pregnancy

Risk Summary

Limited published data from randomized controlled trials, case-controlled trials, and case series do not report a clear association with sildenafil and major birth defects, miscarriage, or adverse maternal or fetal outcomes when sildenafil is used during pregnancy. There are risks to the mother and fetus from untreated pulmonary arterial hypertension (see Clinical Considerations). Animal reproduction studies conducted with sildenafil showed no evidence of embryo-fetal toxicity or teratogenicity at doses up to 32- and 65-times the recommended human dose (RHD) of 20 mg three times a day in rats and rabbits, respectively [See Data].

The estimated background risk of major birth defects and miscarriage for the indicated population is unknown. All pregnancies have a background risk of birth defect, loss, or other adverse outcomes. In the U.S. general population, the estimated background risk of major birth defects and miscarriage in clinically recognized pregnancies is 2–4% and 15–20%, respectively.

Clinical Considerations

Disease-Associated Maternal and/or Embryo/Fetal Risk

Pregnant women with untreated pulmonary arterial hypertension are at risk for heart failure, stroke, preterm delivery, and maternal and fetal death.

Data

Animal Data

No evidence of teratogenicity, embryotoxicity, or fetotoxicity was observed in pregnant rats or rabbits dosed with sildenafil 200 mg/kg/day during organogenesis, a level that is, on a mg/m^2 basis, 32- and 65-times, respectively, the recommended human dose (RHD) of 20 mg three times a day. In a rat pre- and postnatal development study, the no-observed-adverse-effect dose was 30 mg/kg/day (equivalent to 5-times the RHD on a mg/m^2 basis).

8.2 Lactation

Risk Summary

Limited published data from a case report describe the presence of sildenafil and its active metabolite in human milk. There is insufficient information about the effects of sildenafil on the breastfed infant and no information on the effects of sildenafil on milk production. Limited clinical data during lactation preclude a clear determination of the risk of sildenafil to an infant during lactation.

8.4 Pediatric Use

In a randomized, double-blind, multi-center, placebo-controlled, parallel-group, dose-ranging study, 234 patients with PAH, aged 1 to 17 years, body weight greater than or equal to 8 kg, were randomized, on the basis of body weight, to three dose levels of sildenafil, or placebo, for 16 weeks of treatment. Most patients had mild to moderate symptoms at baseline: WHO Functional Class I (32%), II (51%), III (15%), or IV (0.4%). One-third of patients had primary PAH; two-thirds had secondary PAH (systemic-to-pulmonary shunt in 37%; surgical repair in 30%). Sixty-two percent of patients were female. Drug or placebo was administered three times a day.

The primary objective of the study was to assess the effect of sildenafil on exercise capacity as measured by cardiopulmonary exercise testing in pediatric patients developmentally able to perform the test (n = 115). Administration of sildenafil did not result in a statistically significant improvement in exercise capacity in those patients. No patients died during the 16-week controlled study.

After completing the 16-week controlled study, a patient originally randomized to sildenafil remained on his/her dose of sildenafil or, if originally randomized to placebo, was randomized to low-, medium-, or high-dose sildenafil. After all patients completed 16 weeks of follow-up in the controlled study, the blind was broken and doses were adjusted as clinically indicated. Patients treated with sildenafil were followed for a median of 4.6 years (range 2 days to 8.6 years). Mortality during the long-term study, by originally assigned dose, is shown in Figure 6:

Figure 6. Kaplan-Meier Plot of Mortality by Sildenafil Dose

During the study, there were 42 reported deaths, with 37 of these deaths reported prior to a decision to titrate subjects to a lower dosage because of a finding of increased mortality with increasing sildenafil doses. For the survival analysis which included 37 deaths, the hazard ratio for high dose compared to low dose was 3.9, p=0.007. Causes of death were typical of patients with PAH. Use of sildenafil, particularly chronic use, is not recommended in children.

8.5 Geriatric Use

Clinical studies of sildenafil did not include sufficient numbers of subjects aged 65 and over to determine whether they respond differently from younger subjects. Other reported clinical experience has not identified differences in responses between the elderly and younger patients. In general, dose selection for an elderly patient should be cautious, reflecting the greater frequency of decreased hepatic, renal, or cardiac function, and of concomitant disease or other drug therapy [see Clinical Pharmacology (12.3)].

8.6 Patients with Hepatic Impairment

No dose adjustment for mild to moderate impairment is required. Severe impairment has not been studied [see Clinical Pharmacology (12.3)].

8.7 Patients with Renal Impairment

No dose adjustment is required (including severe impairment CLcr < 30 mL/min) [see Clinical Pharmacology (12.3)].

10 OVERDOSAGE

In studies with healthy volunteers of single doses up to 800 mg, adverse events were similar to those seen at lower doses but rates and severities were increased.

In cases of overdose, standard supportive measures should be adopted as required. Renal dialysis is not expected to accelerate clearance as sildenafil is highly bound to plasma proteins and it is not eliminated in the urine.

11 DESCRIPTION

Sildenafil, phosphodiesterase-5 (PDE-5) inhibitor, is the citrate salt of sildenafil, a selective inhibitor of cyclic guanosine monophosphate (cGMP)-specific phosphodiesterase type-5 (PDE-5). Sildenafil is also marketed as VIAGRA® for erectile dysfunction.

Sildenafil citrate is designated chemically as 1-[[3-(6,7-dihydro-1-methyl-7-oxo-3-propyl-1H-pyrazolo [4,3-d] pyrimidin-5-yl)-4-ethoxyphenyl] sulfonyl]-4-methylpiperazine citrate and has the following structural formula:

Sildenafil citrate is a white to off-white crystalline powder with a solubility of 3.5 mg/mL in water and a molecular weight of 666.7.

Sildenafil Tablets: Sildenafil is formulated as white, film-coated round tablets for oral administration. Each tablet contains sildenafil citrate equivalent to 20 mg of sildenafil. In addition to the active ingredient, sildenafil citrate, each tablet contains the following inactive ingredients: microcrystalline cellulose, anhydrous dibasic calcium phosphate, croscarmellose sodium, magnesium stearate, hypromellose, titanium dioxide, lactose monohydrate, and triacetin.

Sildenafil for Oral Suspension: Sildenafil is supplied as white to off-white powders containing 1.57 g of sildenafil citrate (equivalent to 1.12 g sildenafil) in an amber glass bottle intended for reconstitution. Following reconstitution with 90 mL water, the volume of the oral suspension is 112 mL and the oral suspension contains 10 mg/mL sildenafil. The inactive ingredients include sorbitol, citric acid anhydrous, sucralose, sodium citrate dihydrate, xanthan gum, titanium dioxide, sodium benzoate, colloidal silicon dioxide anhydrous and grape flavor. In addition to the bottle, a press-in bottle adapter and an oral dosing syringe (with 0.5 mL and 2 mL dose markings) are provided.

12 CLINICAL PHARMACOLOGY

12.1 Mechanism of Action

Sildenafil is an inhibitor of cGMP specific phosphodiesterase type-5 (PDE-5) in the smooth muscle of the pulmonary vasculature, where PDE-5 is responsible for degradation of cGMP. Sildenafil, therefore, increases cGMP within pulmonary vascular smooth muscle cells resulting in relaxation. In patients with PAH, this can lead to vasodilation of the pulmonary vascular bed and, to a lesser degree, vasodilatation in the systemic circulation.

Studies in vitro have shown that sildenafil is selective for PDE-5. Its effect is more potent on PDE-5 than on other known phosphodiesterases (10-fold for PDE6, greater than 80-fold for PDE1, greater than 700-fold for PDE2, PDE3, PDE4, PDE7, PDE8, PDE9, PDE10, and PDE11). The approximately 4,000-fold selectivity for PDE-5 versus PDE3 is important because PDE3 is involved in control of cardiac contractility. Sildenafil is only about 10-fold as potent for PDE-5 compared to PDE6, an enzyme found in the retina and involved in the phototransduction pathway of the retina. This lower selectivity is thought to be the basis for abnormalities related to color vision observed with higher doses or plasma levels [see Clinical Pharmacology (12.2)].

In addition to pulmonary vascular smooth muscle and the corpus cavernosum, PDE-5 is also found in other tissues including vascular and visceral smooth muscle and in platelets. The inhibition of PDE-5 in these tissues by sildenafil may be the basis for the enhanced platelet anti-aggregatory activity of nitric oxide observed in vitro, and the mild peripheral arterial-venous dilatation in vivo.

12.2 Pharmacodynamics

Effects of Sildenafil on Hemodynamic Measures

Patients on all sildenafil doses achieved a statistically significant reduction in mean pulmonary arterial pressure (mPAP) compared to those on placebo in a study with no background vasodilators [Study 1 in Clinical Studies (14)]. Data on other hemodynamic measures for the sildenafil 20 mg three times a day and placebo dosing regimens is displayed in Table 3. The relationship between these effects and improvements in 6-minute walk distance is unknown.

Table 3. Changes from Baseline in Hemodynamic Parameters at Week 12 [mean (95% CI)] for the Sildenafil 20 mg Three Times a Day and Placebo Group
 | Placebo (n = 65) [The number of patients per treatment group varied slightly for each parameter due to missing assessments.] | Sildenafil 20 mg three times a day (n = 65)
mPAP (mmHg) | 0.6 (-0.8, 2.0) | -2.1 (-4.3, 0.0)
PVR (dyn∙s/cm^5) | 49 (-54, 153) | -122 (-217, -27)
SVR (dyn∙s/cm^5) | -78 (-197, 41) | -167 (-307, -26)
RAP (mmHg) | 0.3 (-0.9, 1.5) | -0.8 (-1.9, 0.3)
CO (L/min) | -0.1 (-0.4, 0.2) | 0.4 (0.1, 0.7)
HR (beats/min) | -1.3 (-4.1, 1.4) | -3.7 (-5.9, -1.4)
mPAP = mean pulmonary arterial pressure; PVR= pulmonary vascular resistance; SVR = systemic vascular resistance; RAP = right atrial pressure; CO = cardiac output; HR = heart rate

In another study evaluating lower doses of sildenafil 1 mg, 5 mg and 20 mg [Study 3 in Clinical Studies (14)], there were no significant differences in the effects on hemodynamic variables between doses.

Effects of Sildenafil on Blood Pressure

Single oral doses of sildenafil 100 mg administered to healthy volunteers produced decreases in supine blood pressure (mean maximum decrease in systolic/diastolic blood pressure of 8/5 mmHg). The decrease in blood pressure was most notable approximately 1–2 hours after dosing, and was not different from placebo at 8 hours. Similar effects on blood pressure were noted with 25 mg, 50 mg and 100 mg doses of sildenafil, therefore the effects are not related to dose or plasma levels within this dosage range. Larger effects were recorded among patients receiving concomitant nitrates [see Contraindications (4)].

Single oral doses of sildenafil up to 100 mg in healthy volunteers produced no clinically relevant effects on ECG. After chronic dosing of 80 mg three times a day to patients with PAH, no clinically relevant effects on ECG were reported.

After chronic dosing of 80 mg three times a day sildenafil to healthy volunteers, the largest mean change from baseline in supine systolic and supine diastolic blood pressures was a decrease of 9.0 mmHg and 8.4 mmHg, respectively.

After chronic dosing of 80 mg three times a day sildenafil to patients with systemic hypertension, the mean change from baseline in systolic and diastolic blood pressures was a decrease of 9.4 mmHg and 9.1 mmHg, respectively.

After chronic dosing of 80 mg three times a day sildenafil to patients with PAH, lesser reductions than above in systolic and diastolic blood pressures were observed (a decrease in both of 2 mmHg).

Effects of Sildenafil on Vision

At single oral doses of 100 mg and 200 mg, transient dose-related impairment of color discrimination (blue/green) was detected using the Farnsworth-Munsell 100-hue test, with peak effects near the time of peak plasma levels. This finding is consistent with the inhibition of PDE6, which is involved in phototransduction in the retina. An evaluation of visual function at doses up to 200 mg revealed no effects of sildenafil on visual acuity, intraocular pressure, or pupillometry.

12.3 Pharmacokinetics

Absorption and Distribution

Sildenafil is rapidly absorbed after oral administration, with a mean absolute bioavailability of 41% (25–63%). Maximum observed plasma concentrations are reached within 30 to 120 minutes (median 60 minutes) of oral dosing in the fasted state. When sildenafil is taken with a high-fat meal, the rate of absorption is reduced, with a mean delay in Tmax of 60 minutes and a mean reduction in Cmax of 29%. The mean steady state volume of distribution (Vss) for sildenafil is 105 L, indicating distribution into the tissues. Sildenafil and its major circulating N-desmethyl metabolite are both approximately 96% bound to plasma proteins. Protein binding is independent of total drug concentrations.

Bioequivalence was established between the 20 mg tablet and the 10 mg/mL oral suspension when administered as a 20 mg single oral dose of sildenafil (as citrate).

Metabolism and Excretion

Sildenafil is cleared predominantly by the CYP3A (major route) and cytochrome P450 2C9 (CYP2C9, minor route) hepatic microsomal isoenzymes. The major circulating metabolite results from N-desmethylation of sildenafil, and is, itself, further metabolized. This metabolite has a phosphodiesterase selectivity profile similar to sildenafil and an in vitro potency for PDE-5 approximately 50% of the parent drug. In healthy volunteers, plasma concentrations of this metabolite are approximately 40% of those seen for sildenafil, so that the metabolite accounts for about 20% of sildenafil's pharmacologic effects. In patients with PAH, however, the ratio of the metabolite to sildenafil is higher. Both sildenafil and the active metabolite have terminal half-lives of about 4 hours.

After oral administration, sildenafil is excreted as metabolites predominantly in the feces (approximately 80% of the administered oral dose) and to a lesser extent in the urine (approximately 13% of the administered oral dose).

Population Pharmacokinetics

Age, gender, race, and renal and hepatic function were included as factors assessed in the population pharmacokinetic model to evaluate sildenafil pharmacokinetics in patients with PAH. The dataset available for the population pharmacokinetic evaluation contained a wide range of demographic data and laboratory parameters associated with hepatic and renal function. None of these factors had a significant impact on sildenafil pharmacokinetics in patients with PAH.

In patients with PAH, the average steady-state concentrations were 20–50% higher when compared to those of healthy volunteers. There was also a doubling of Cmin levels compared to healthy volunteers. Both findings suggest a lower clearance and/or a higher oral bioavailability of sildenafil in patients with PAH compared to healthy volunteers.

Geriatric Patients

Healthy elderly volunteers (65 years or over) had a reduced clearance of sildenafil, resulting in approximately 84% and 107% higher plasma concentrations of sildenafil and its active N-desmethyl metabolite, respectively, compared to those seen in healthy younger volunteers (18–45 years). Due to age-differences in plasma protein binding, the corresponding increase in the AUC of free (unbound) sildenafil and its active N-desmethyl metabolite were 45% and 57%, respectively.

Renal Impairment

In volunteers with mild (CLcr = 50–80 mL/min) and moderate (CLcr = 30–49 mL/min) renal impairment, the pharmacokinetics of a single oral dose of sildenafil (50 mg) was not altered. In volunteers with severe (CLcr less than 30 mL/min) renal impairment, sildenafil clearance was reduced, resulting in approximately doubling of AUC and Cmax compared to age-matched volunteers with no renal impairment. In addition, N-desmethyl metabolite AUC and Cmax values were significantly increased 200 % and 79 %, respectively, in subjects with severe renal impairment compared to subjects with normal renal function.

Hepatic Impairment

In volunteers with mild to moderate hepatic cirrhosis (Child-Pugh class A and B), sildenafil clearance was reduced, resulting in increases in AUC (84%) and Cmax (47%) compared to age-matched volunteers with no hepatic impairment. Patients with severe hepatic impairment (Child-Pugh class C) have not been studied.

Drug Interaction Studies

In vitro studies

Sildenafil metabolism is principally mediated by the CYP3A (major route) and CYP2C9 (minor route) cytochrome P450 isoforms. Therefore, inhibitors of these isoenzymes may reduce sildenafil clearance and inducers of these isoenzymes may increase sildenafil clearance.

Sildenafil is a weak inhibitor of the cytochrome P450 isoforms 1A2, 2C9, 2C19, 2D6, 2E1 and 3A (IC50 greater than 150 µM).

Sildenafil is not expected to affect the pharmacokinetics of compounds which are substrates of these CYP enzymes at clinically relevant concentrations.

In vivo studies

The effects of other drugs on sildenafil pharmacokinetics and the effects of sildenafil on the exposure to other drugs are shown in Figure 7 and Figure 8, respectively.

Figure 7. Effects of Other Drugs on Sildenafil Pharmacokinetics

Figure 8. Effects of Sildenafil on Other Drugs

CYP3A Inhibitors and Beta Blockers

Population pharmacokinetic analysis of data from patients in clinical trials indicated an approximately 30% reduction in sildenafil clearance when it was co-administered with mild/moderate CYP3A inhibitors and an approximately 34% reductions in sildenafil clearance when co-administered with beta-blockers. Sildenafil exposure at a dose of 80 mg three times a day without concomitant medication is shown to be 5-fold the exposure at a dose of 20 mg three times a day. This concentration range covers the same increased sildenafil exposure observed in specifically-designed drug interaction studies with CYP3A inhibitors (except for potent inhibitors such as ketoconazole, itraconazole, and ritonavir).

CYP3A4 inducers including bosentan

Concomitant administration of potent CYP3A inducers is expected to cause substantial decreases in plasma levels of sildenafil.

Population pharmacokinetic analysis of data from patients in clinical trials indicated approximately 3-fold the sildenafil clearance when it was co-administered with mild CYP3A inducers.

Epoprostenol

The mean reduction of sildenafil (80 mg three times a day) bioavailability when co-administered with epoprostenol was 28%, resulting in about 22% lower mean average steady state concentrations. Therefore, the slight decrease of sildenafil exposure in the presence of epoprostenol is not considered clinically relevant. The effect of sildenafil on epoprostenol pharmacokinetics is not known.

No significant interactions were shown with tolbutamide (250 mg) or warfarin (40 mg), both of which are metabolized by CYP2C9.

Alcohol

Sildenafil (50 mg) did not potentiate the hypotensive effect of alcohol in healthy volunteers with mean maximum blood alcohol levels of 0.08%.

13 NONCLINICAL TOXICOLOGY

13.1 Carcinogenesis, Mutagenesis, Impairment of Fertility

Sildenafil was not carcinogenic when administered to rats for up to 24 months at 60 mg/kg/day, a dose resulting in total systemic exposure (AUC) to unbound sildenafil and its major metabolite 33- and 37-times, for male and female rats respectively, the human exposure at the RHD of 20 mg three times a day. Sildenafil was not carcinogenic when administered to male and female mice for up to 21 and 18 months, respectively, at doses up to a maximally tolerated level of 10 mg/kg/day, a dose equivalent to the RHD on a mg/m^2 basis.

Sildenafil was negative in in vitro bacterial and Chinese hamster ovary cell assays to detect mutagenicity, and in vitro human lymphocytes and in vivo mouse micronucleus assays to detect clastogenicity.

There was no impairment of fertility in male or female rats given up to 60 mg sildenafil/kg/day, a dose producing a total systemic exposure (AUC) to unbound sildenafil and its major metabolite of 19- and 38- times for males and females, respectively, the human exposure at the RHD of 20 mg three times a day.

14 CLINICAL STUDIES

Studies of Adults with Pulmonary Arterial Hypertension

Study 1 (Sildenafil monotherapy (20 mg, 40 mg, and 80 mg three times a day))

A randomized, double-blind, placebo-controlled study of sildenafil (Study 1) was conducted in 277 patients with PAH (defined as a mean pulmonary artery pressure of greater than or equal to 25 mmHg at rest with a pulmonary capillary wedge pressure less than 15 mmHg). Patients were predominantly World Health Organization (WHO) functional classes II–III. Allowed background therapy included a combination of anticoagulants, digoxin, calcium channel blockers, diuretics, and oxygen. The use of prostacyclin analogues, endothelin receptor antagonists, and arginine supplementation were not permitted. Subjects who had failed to respond to bosentan were also excluded. Patients with left ventricular ejection fraction less than 45% or left ventricular shortening fraction less than 0.2 also were not studied.

Patients were randomized to receive placebo (n=70) or sildenafil 20 mg (n = 69), 40 mg (n = 67) or 80 mg (n = 71) three times a day for a period of 12 weeks. They had either primary pulmonary hypertension (PPH) (63%), PAH associated with CTD (30%), or PAH following surgical repair of left-to-right congenital heart lesions (7%). The study population consisted of 25% men and 75% women with a mean age of 49 years (range: 18–81 years) and baseline 6-minute walk distance between 100 and 450 meters (mean 343).

The primary efficacy endpoint was the change from baseline at week 12 (at least 4 hours after the last dose) in the 6-minute walk distance. Placebo-corrected mean increases in walk distance of 45–50 meters were observed with all doses of sildenafil. These increases were significantly different from placebo, but the sildenafil dose groups were not different from each other (see Figure 9), indicating no additional clinical benefit from doses higher than 20 mg three times a day. The improvement in walk distance was apparent after 4 weeks of treatment and was maintained at week 8 and week 12.

Figure 9. Change from Baseline in 6-Minute Walk Distance (meters) at Weeks 4, 8, and 12 in Study 1: Mean (95% Confidence Interval)

Figure 10 displays subgroup efficacy analyses in Study 1 for the change from baseline in 6-Minute Walk Distance at Week 12 including baseline walk distance, disease etiology, functional class, gender, age, and hemodynamic parameters.

Figure 10. Placebo Corrected Change From Baseline in 6-Minute Walk Distance (meters) at Week 12 by study subpopulation in Study 1: Mean (95% Confidence Interval)

Key: PAH = pulmonary arterial hypertension; CTD = connective tissue disease; PH = pulmonary hypertension;
PAP = pulmonary arterial pressure; PVRI = pulmonary vascular resistance index; TID = three times daily.

Of the 277 treated patients, 259 entered a long-term, uncontrolled extension study. At the end of 1 year, 94% of these patients were still alive. Additionally, walk distance and functional class status appeared to be stable in patients taking sildenafil. Without a control group, these data must be interpreted cautiously.

Study 2 (Sildenafil co-administered with epoprostenol)

A randomized, double-blind, placebo controlled study (Study 2) was conducted in 267 patients with PAH who were taking stable doses of intravenous epoprostenol. Patients had to have a mean pulmonary artery pressure (mPAP) greater than or equal to 25 mmHg and a pulmonary capillary wedge pressure (PCWP) less than or equal to 15 mmHg at rest via right heart catheterization within 21 days before randomization, and a baseline 6-minute walk test distance greater than or equal to 100 meters and less than or equal to 450 meters (mean 349 meters). Patients were randomized to placebo or sildenafil (in a fixed titration starting from 20 mg, to 40 mg and then 80 mg, three times a day) and all patients continued intravenous epoprostenol therapy.

At baseline patients had PPH (80%) or PAH secondary to CTD (20%); WHO functional class I (1%), II (26%), III (67%), or IV (6%); and the mean age was 48 years, 80% were female, and 79% were Caucasian.

There was a statistically significant greater increase from baseline in 6-minute walk distance at Week 16 (primary endpoint) for the sildenafil group compared with the placebo group. The mean change from baseline at Week 16 (last observation carried forward) was 30 meters for the sildenafil group compared with 4 meters for the placebo group giving an adjusted treatment difference of 26 meters (95% CI: 10.8, 41.2) (p = 0.0009).

Patients on sildenafil achieved a statistically significant reduction in mPAP compared to those on placebo. A mean placebo-corrected treatment effect of -3.9 mmHg was observed in favor of sildenafil (95% CI: -5.7, -2.1) (p = 0.00003).

Time to clinical worsening of PAH was defined as the time from randomization to the first occurrence of a clinical worsening event (death, lung transplantation, initiation of bosentan therapy, or clinical deterioration requiring a change in epoprostenol therapy). Table 4 displays the number of patients with clinical worsening events in Study 2. Kaplan-Meier estimates and a stratified log-rank test demonstrated that placebo-treated patients were 3 times more likely to experience a clinical worsening event than sildenafil-treated patients and that sildenafil-treated patients experienced a significant delay in time to clinical worsening versus placebo-treated patients (p = 0.0074). Kaplan-Meier plot of time to clinical worsening is presented in Figure 11.

Table 4. Clinical Worsening Events in Study 2
 | Placebo (N = 131) |  | Sildenafil (N = 134)
Number of subjects with clinical worsening first event | 23 |  | 8
 | First Event | All Events | First Event | All Events
Death, n | 3 | 4 | 0 | 0
Lung Transplantation, n | 1 | 1 | 0 | 0
Hospitalization due to PAH, n | 9 | 11 | 8 | 8
Clinical deterioration resulting in:
Change of Epoprostenol Dose, n | 9 | 16 | 0 | 2
Initiation of Bosentan, n | 1 | 1 | 0 | 0
Proportion Worsened 95% Confidence Interval | 0.187 (0.12 – 0.26) |  | 0.062 (0.02 – 0.10)

Figure 11. Kaplan-Meier Plot of Time (in Days) to Clinical Worsening of PAH in Study 2

Improvements in WHO functional class for PAH were also demonstrated in subjects on sildenafil compared to placebo. More than twice as many sildenafil-treated patients (36%) as placebo-treated patients (14%) showed an improvement in at least one functional New York Heart Association (NYHA) class for PAH.

Study 3 (Sildenafil monotherapy (1 mg, 5 mg, and 20 mg three times a day))

A randomized, double-blind, parallel dose study (Study 3) was planned in 219 patients with PAH. This study was prematurely terminated with 129 subjects enrolled. Patients were required to have a mPAP greater than or equal to 25 mmHg and a PCWP less than or equal to 15 mmHg at rest via right heart catheterization within 12 weeks before randomization, and a baseline 6-minute walk test distance greater than or equal to 100 meters and less than or equal to 450 meters (mean 345 meters). Patients were randomized to 1 of 3 doses of sildenafil: 1 mg, 5 mg, and 20 mg, three times a day.

At baseline patients had PPH (74%) or secondary PAH (26%); WHO functional class II (57%), III (41%), or IV (2%); the mean age was 44 years; and 67% were female. The majority of subjects were Asian (67%), and 28% were Caucasian.

The primary efficacy endpoint was the change from baseline at Week 12 (at least 4 hours after the last dose) in the 6-minute walk distance. Similar increases in walk distance (mean increase of 38–41 meters) were observed in the 5 and 20 mg dose groups. These increases were significantly better than those observed in the 1 mg dose group (Figure 12).

Figure 12. Mean Change from Baseline in Six Minute Walk (meters) by Visit to Week 12 – ITT Population

Sildenafil Protocol A1481244

Study 4 (Sildenafil added to bosentan therapy – lack of effect on exercise capacity)

A randomized, double-blind, placebo controlled study was conducted in 103 patients with PAH who were on bosentan therapy for a minimum of three months. The PAH patients included those with primary PAH, and PAH associated with CTD. Patients were randomized to placebo or sildenafil (20 mg three times a day) in combination with bosentan (62.5–125 mg twice a day). The primary efficacy endpoint was the change from baseline at Week 12 in 6MWD. The results indicate that there is no significant difference in mean change from baseline on 6MWD observed between sildenafil 20 mg plus bosentan and bosentan alone.

16 HOW SUPPLIED/STORAGE AND HANDLING

Product: 50436-0034

NDC: 50436-0034-1 1 TABLET, FILM COATED in a POUCH

NDC: 50436-0034-2 2 TABLET, FILM COATED in a POUCH

NDC: 50436-0034-3 3 TABLET, FILM COATED in a POUCH

NDC: 50436-0034-4 4 TABLET, FILM COATED in a POUCH

NDC: 50436-0034-5 5 TABLET, FILM COATED in a POUCH

17 PATIENT COUNSELING INFORMATION

See FDA-approved patient labeling (Patient Information)

- Inform patients of contraindication of sildenafil with regular and/or intermittent use of organic nitrates.
- Inform patients that sildenafil is also marketed as VIAGRA for erectile dysfunction. Advise patients taking sildenafil not to take VIAGRA or other PDE-5 inhibitors.
- Advise patients to seek immediate medical attention for a sudden loss of vision in one or both eyes while taking sildenafil. Such an event may be a sign of NAION.
- Advise patients to seek prompt medical attention in the event of sudden decrease or loss of hearing while taking sildenafil. These events may be accompanied by tinnitus and dizziness.

This product's label may have been updated. For current full prescribing information, please visit www.greenstonellc.com.

LAB-0562-8.0

PATIENT INFORMATION

Sildenafil tablets

Sildenafil oral suspension

Read this Patient Information before you start taking sildenafil and each time you get a refill. There may be new information. This information does not take the place of talking with your doctor about your medical condition or treatment. If you have any questions about sildenafil, ask your doctor or pharmacist.

What is the most important information I should know about sildenafil?

Never take sildenafil with any nitrate or guanylate cyclase stimulator medicines. Your blood pressure could drop quickly to an unsafe level.

Nitrate medicines include:

- Medicines that treat chest pain (angina)
- Nitroglycerin in any form including tablets, patches, sprays, and ointments
- Isosorbide mononitrate or dinitrate
- Street drugs called "poppers" (amyl nitrate or nitrite)

Guanylate cyclase stimulators include:

- Riociguat (Adempas)

Ask your doctor or pharmacist if you are not sure if you are taking a nitrate or a guanylate cyclase stimulator medicine.

What is sildenafil?

Sildenafil is a prescription medicine used in adults to treat pulmonary arterial hypertension (PAH). With PAH, the blood pressure in your lungs is too high. Your heart has to work hard to pump blood into your lungs.

Sildenafil improves the ability to exercise and can slow down worsening changes in your physical condition.

- Sildenafil is not for use in children
- Adding sildenafil to another medication used to treat PAH bosentan (Tracleer®), does not result in improvement in your ability to exercise.

Sildenafil contains the same medicine as VIAGRA® (sildenafil), which is used to treat erectile dysfunction (impotence). Do not take sildenafil with VIAGRA or other PDE-5 inhibitors.

Who should not take Sildenafil?

Do not take sildenafil if you:

- take nitrate medicines. See "What is the most important information I should know about sildenafil?"
- take guanylate cyclase stimulator medicines. See "What is the most important information I should know about sildenafil?"
- are allergic to sildenafil or any other ingredient in sildenafil tablets or oral suspension. See "What are the ingredients in sildenafil tablets and oral suspension?" at the end of this leaflet.

What should I tell my doctor before taking sildenafil?

Tell your doctor about all of your medical conditions, including if you

- have heart problems such as angina (chest pain), heart failure, irregular heartbeats, or have had a heart attack
- have a disease called pulmonary veno-occlusive disease (PVOD)
- have high or low blood pressure or blood circulation problems
- have an eye problem called retinitis pigmentosa
- have or had loss of sight in one or both eyes
- have any problem with the shape of your penis or Peyronie's disease
- have any blood cell problems such as sickle cell anemia
- have a stomach ulcer or any bleeding problems
- are pregnant or planning to become pregnant. It is not known if sildenafil could harm your unborn baby.
- are breastfeeding. Sildenafil passes into your breast milk, it is not known if it could harm your baby.

Tell your doctor about all of the medicines you take, including prescription and non-prescription medicines, vitamins, and herbal products. Sildenafil and certain other medicines can cause side effects if you take them together. The doses of some of your medicines may need to be adjusted while you take sildenafil.

Especially tell your doctor if you take

- Nitrate medicines. See "What is the most important information I should know about sildenafil?"
- Riociguat (Adempas). See "What is the most important information I should know about sildenafil?"
- Ritonavir (Norvir®) or other medicines used to treat HIV infection
- Ketoconazole (Nizoral®)
- Itraconazole (Sporanox)
- High blood pressure medicine

Know the medicines you take. Keep a list of your medicines and show it to your doctor and pharmacist when you get a new medicine.

How should I take sildenafil?

- Take sildenafil exactly as your doctor tells you.

Sildenafil may be prescribed to you as

- Sildenafil tablets or sildenafil oral suspension
- Take sildenafil tablet or oral suspension 3 times a day about 4 to 6 hours apart.
- Take sildenafil tablets or oral suspension at the same times every day.
- Sildenafil oral suspension will be mixed for you by your pharmacist. Do not mix sildenafil oral suspension with other medicine or flavoring. Shake well for at least 10 seconds before each dose.
- If you miss a dose, take it as soon as you remember. If it is close to your next dose, skip the missed dose, and take your next dose at the regular time.
- Do not take more than one dose of sildenafil at a time.
- Do not change your dose or stop taking sildenafil on your own. Talk to your doctor first.
- If you take too much sildenafil, call your doctor or go to the nearest hospital emergency room.

What are the possible side effects of sildenafil?

- low blood pressure. Low blood pressure may cause you to feel faint or dizzy. Lie down if you feel faint or dizzy.
- more shortness of breath than usual. Tell your doctor if you get more short of breath after you start sildenafil. More shortness of breath than usual may be due to your underlying medical condition.
- decreased eyesight or loss of sight in one or both eyes (NAION). If you notice a sudden decrease or loss of eyesight, talk to your doctor right away.
- sudden decrease or loss of hearing. If you notice a sudden decrease or loss of hearing, talk to your doctor right away. It is not possible to determine whether these events are related directly to this class of oral medicines, including sildenafil, or to other diseases or medicines, to other factors, or to a combination of factors.
- heart attack, stroke, irregular heartbeats, and death. Most of these happened in men who already had heart problems.
- erections that last several hours. If you have an erection that lasts more than 4 hours, get medical help right away. If it is not treated right away, priapism can permanently damage your penis.

The most common side effects with sildenafil include:

Nosebleed, headache, upset stomach, getting red or hot in the face (flushing), trouble sleeping, as well as fever, erection increased, respiratory infection, nausea, vomiting, bronchitis, pharyngitis, runny nose, and pneumonia in children.

Tell your doctor if you have any side effect that bothers you or doesn't go away.

These are not all the possible side effects of sildenafil. For more information, ask your doctor or pharmacist.

Call your doctor for medical advice about side effects. You may report side effects to FDA at 1-800-FDA-1088.

How should I store sildenafil?

- Store sildenafil tablets at controlled room temperature, between 20°C – 25°C (68°F to 77°F).
- Store sildenafil reconstituted oral suspension below 30°C (86°F) or in a refrigerator between 2°C to 8°C (36°F to 46°F).
- Do not freeze sildenafil oral suspension.
- Throw away sildenafil oral suspension after 60 days.
- Keep sildenafil and all medicines away from children.

General information about sildenafil

Medicines are sometimes prescribed for purposes that are not in the patient leaflet. Do not use sildenafil for a condition for which it was not prescribed. Do not give sildenafil to other people, even if they have the same symptoms you have. It could harm them.

This patient leaflet summarizes the most important information about sildenafil. If you would like more information about sildenafil talk with your doctor. You can ask your doctor or pharmacist for information about sildenafil that is written for health professionals.

For more information go to www.greenstonellc.com or call 1-800-438-1985.

What are the ingredients in sildenafil tablets and oral suspension?

Sildenafil tablets

Active ingredients: sildenafil citrate

Inactive ingredients: microcrystalline cellulose, anhydrous dibasic calcium phosphate, croscarmellose sodium, magnesium stearate, hypromellose, titanium dioxide, lactose monohydrate, and triacetin

Sildenafil for oral suspension

Active ingredients: sildenafil citrate

Inactive ingredients: sorbitol, citric acid anhydrous, sucralose, sodium citrate dihydrate, xanthan gum, titanium dioxide, sodium benzoate, colloidal silicon dioxide anhydrous, and grape flavor

This product's label may have been updated. For current full prescribing information, please visit www.greenstonellc.com.

This Patient Information has been approved by the U.S. Food and Drug Administration.

LAB-0563-7.0
Revised: February 2020

Instructions for Use

Sildenafil oral suspension

Read this Instructions for Use for sildenafil oral suspension before you start taking and each time you get a refill. There may be new information. This information does not take the place of talking to your doctor about your medical condition or your treatment.

Important information:

- Your pharmacist should tell you how to measure sildenafil oral suspension by using the oral syringe provided in the pack.
- Sildenafil oral suspension should only be given using the oral syringe supplied with each pack.
- Sildenafil for oral suspension should not be mixed with any other medicine or flavoring.

Supplies you will need to take sildenafil oral suspension:

- Bottle of sildenafil oral suspension with syringe adaptor fitted in neck of bottle
- Oral syringe (as supplied by pharmacist). (See Figure A)

Figure A

1. Shake the bottle of sildenafil oral suspension for 10 seconds before each use. (See Figure B)
2. Remove the cap. Open the bottle by pushing downward on the cap and twisting it in the direction of the arrow (counter-clockwise). (See Figure B)
  Figure B
3. Insert the tip of the oral syringe into the adaptor while the bottle is upright, on a flat surface. Fully push down (depress) the plunger of the syringe. (See Figure C)
  Figure C
4. Turn the bottle upside down while holding the oral syringe in place. Slowly pull back the plunger of the oral syringe until the bottom of the plunger is even with the graduation markings on the syringe for the prescribed dose for you. Take your dose of sildenafil oral suspension exactly as prescribed by your doctor. If air bubbles can be seen, slowly push the oral suspension in the syringe back into the bottle. Repeat steps 3 and 4. (See Figure D)
  Figure D
5. Turn the bottle back upright with the oral syringe still in place. Remove the oral syringe from the bottle by pulling straight up on the barrel of the oral dosing syringe. (See Figure E)
  Figure E
6. Put the tip of the oral syringe into your mouth. Point the tip of the oral syringe towards the inside of the cheek. Slowly push down the plunger of the oral syringe. (See Figure F)
  Figure F
7. Replace the cap on the bottle, leaving the bottle adaptor in place. Wash the oral syringe as instructed below.
8. The syringe should be washed after each dose. Pull the plunger out of the barrel and rinse both parts with water. (See Figure G)
  Figure G
9. Dry all parts with a clean paper towel. Push the plunger back into the barrel. Store the syringe with sildenafil oral suspension in a clean safe place.

Administer sildenafil oral suspension using the oral syringe supplied with each pack. Refer to the patient instructions for use for more detailed instructions for use. Discard any unused suspension after the expiration date written on the bottle.

How should I store sildenafil?

- Store sildenafil reconstituted oral suspension below 30°C (86°F) or in a refrigerator between 2°C to 8°C (36°F to 46°F).
- Do not freeze sildenafil oral suspension
- Throw away (discard) sildenafil oral suspension after 60 days.
- Keep sildenafil and all medicines away from children.

This Instruction for Use has been approved by the U.S. Food and Drug Administration.

This product's label may have been updated. For current full prescribing information, please visit www.greenstonellc.com

LAB-0959-2.0
Revised: February 2020